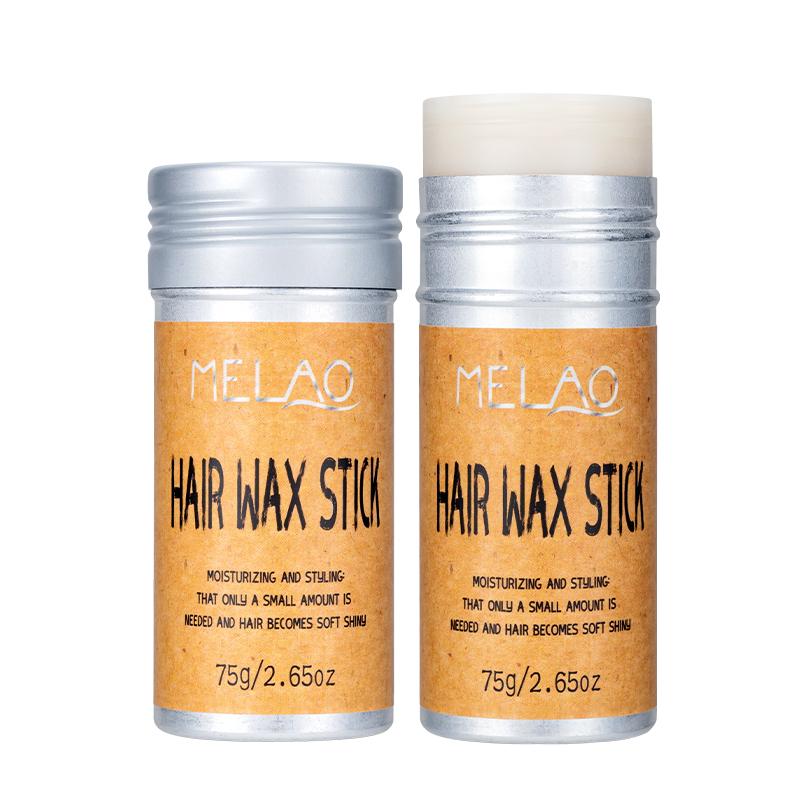 DRUG LABEL: MELAO Hair Wax Stick
NDC: 83566-591 | Form: STICK
Manufacturer: Guangzhou Yilong Cosmetics Co., Ltd
Category: otc | Type: HUMAN OTC DRUG LABEL
Date: 20240827

ACTIVE INGREDIENTS: GLYCERIN 2.4 g/100 g
INACTIVE INGREDIENTS: CARNAUBA WAX 15 g/100 g; MAGNESIUM DISODIUM EDTA 2.3 g/100 g; PROPYLENE GLYCOL 1-STEARATE 2 g/100 g; PROPYLPARABEN 3.6 g/100 g; PEG-15 GLYCERYL STEARATE 16 g/100 g; PENTAMETHYL CYCLOPENTASILOXANE 4 g/100 g; BUTYROSPERMUM PARKII (SHEA) BUTTER UNSAPONIFIABLES 16 g/100 g; AROMADENDRIN 0.9 g/100 g; SODIUM POLYACRYLATE (8000 MW) 1 g/100 g; CETEARYL BEHENATE 18.1 g/100 g; PETROLATUM 15 g/100 g; METHYLPARABEN 3.6 g/100 g

MELAO Hair Wax Stick

Active ingredients

GLYCERIN 2.40%

Inactive ingredients

GLYCERYL STEARATE 16%

CETEARYL ALCOHOL 18.1%

BUTYROSPERMUM PARKII (SHEA) BUTTER 16%

PEG-12 CARNAUBA 15%

PETROLATUM 15%

CYCLOPENTASILOXANE 4%

METHYLPARABEN 3.70%

PROPYLPARABEN 3.60%

DISODIUM EDTA 2.30%

PROPYLENE GLYCOL 2%

SODIUM POLYACRYLATE 1%

AROMA 0.90%

Purpose

Moisture

Uses

Step 1: Clean and thoroughly dry your hair.

Step 2: Rotate the bottle cap to open the product.

Step 3: Gently apply to the surface of the hair.

Stop use and ask a doctor if

rash occurs.

Do not use

on damaged or broken skin.

When using this product

keep out of eyes. Rinse withwater to remove.

Keep out of reach of children.

If swallowed, get medical help or contact a Poison Control Center right away.

DOSAGE & ADMINISTRATION

Squeeze out an appropriate amount of product and spread evenly on skin.

Stop use and ask a doctor if

rash occurs.